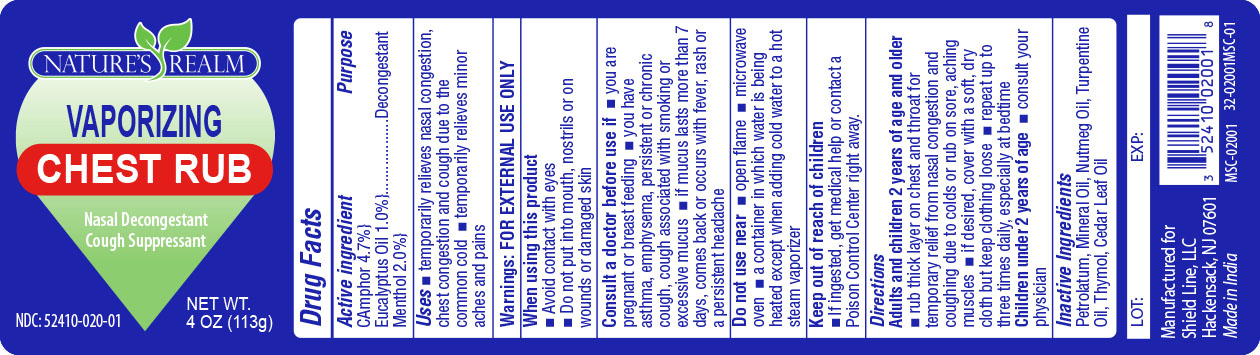 DRUG LABEL: NATURES REALM VAPORIZING CHEST RUB
NDC: 52410-0200 | Form: GEL
Manufacturer: Shield Line LLC
Category: otc | Type: HUMAN OTC DRUG LABEL
Date: 20210224

ACTIVE INGREDIENTS: CAMPHOR (SYNTHETIC) 5.3 g/113 g; EUCALYPTUS OIL 1.13 g/113 g; MENTHOL 2.26 g/113 g
INACTIVE INGREDIENTS: PETROLATUM; MINERAL OIL; NUTMEG OIL; TURPENTINE OIL; THYMOL; CEDAR LEAF OIL

Active Ingredients

Camphor 4.7 % Eucalyptus Oil 1% Menthol 2%

Purpose

Decongestant

Uses

- temporarily relieves nasal congestion, chest congestion, and cough due to the common cold
- temporarily relieves minor aches and pains

Warnings:

FOR EXTERNAL USE ONLY

When using this product

- Avoid contact with eyes
- Do not put into mouth, nostrils or on wounds or damaged skin

Consult a doctor before use if

- you are pregnant or breast feeding
- you have ashtma, emphysema, persistent or chronic cough, cough associated with smoking or excessive mucus
- If mucus lasts more than 7 days, comes back or occurs with fever, rash or a persistent headache

Do not use near

- open flame
- microwave oven
- a container in which water is being heated except when adding cold water to a hot stream vaporizer

Keep out of reach of children

- If ingested, get medical help or contract a Poison Control Center right away

Directions

Adults and children 2 years of age and older

- rub thick layer on chest and throat for temporary relief from nasal congestion and coughing due to colds or rub on sore aching muscles
- If desired, cover with a soft dry cloth but keep clothing loose
- repeat up to three times daily especially at bedtime

Children under 2 years of age

- consult your physician

Inactive Ingredients

Petrolatum, Mineral Oil, Nutmeg Oil, Turpentine Oil, Thymol, Cedar Leaf Oil